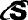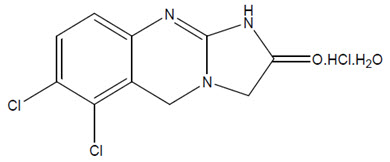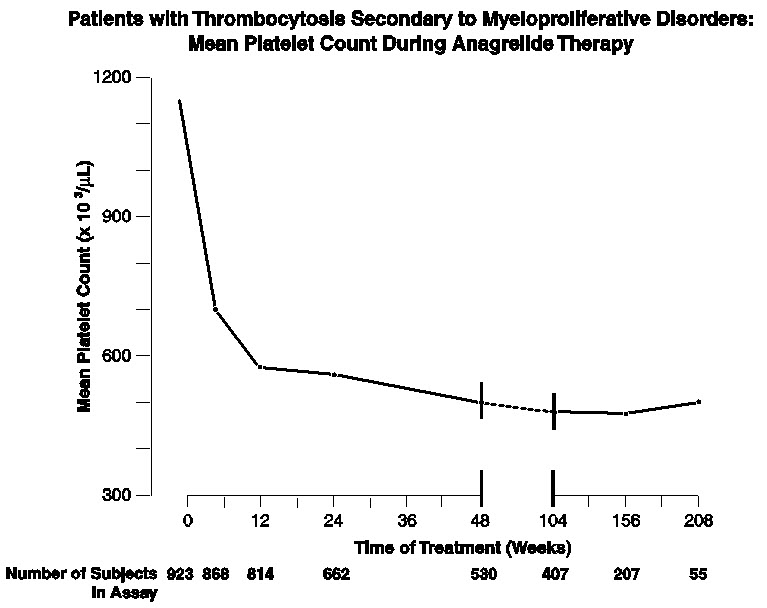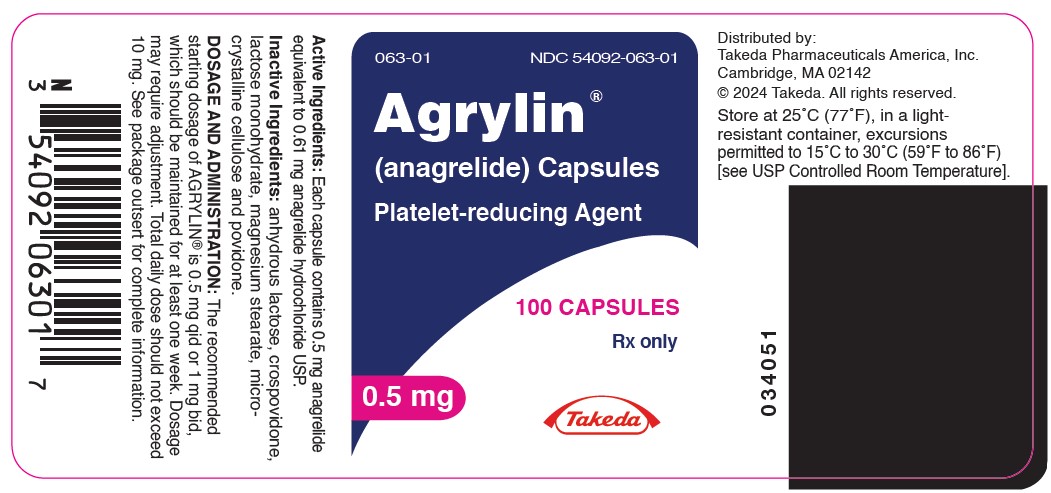 DRUG LABEL: Agrylin
NDC: 54092-063 | Form: CAPSULE
Manufacturer: Takeda Pharmaceuticals America, Inc.
Category: prescription | Type: HUMAN PRESCRIPTION DRUG LABEL
Date: 20241031

ACTIVE INGREDIENTS: ANAGRELIDE HYDROCHLORIDE ANHYDROUS 0.5 mg/1 1
INACTIVE INGREDIENTS: ANHYDROUS LACTOSE; CROSPOVIDONE; LACTOSE MONOHYDRATE; MAGNESIUM STEARATE; MICROCRYSTALLINE CELLULOSE; POVIDONE K30

HIGHLIGHTS OF PRESCRIBING INFORMATION

These highlights do not include all the information needed to use AGRYLIN safely and effectively. See full prescribing information for AGRYLIN.
AGRYLIN® (anagrelide) capsules, for oral use
Initial U.S. Approval: 1997

1 INDICATIONS AND USAGE

AGRYLIN is a platelet reducing agent indicated for the treatment of thrombocythemia, secondary to myeloproliferative neoplasms, to reduce the elevated platelet count and the risk of thrombosis and to ameliorate associated symptoms including thrombo-hemorrhagic events. (1)

2 DOSAGE AND ADMINISTRATION

- The starting dose for adults is 0.5 mg four times a day or 1 mg twice a day. (2.1)
- The starting dose for pediatric patients is 0.5 mg per day. (2.1)
- Maintain the starting dose for at least one week and then titrate to maintain target platelet counts. (2.2)
- Do not exceed a dose increment of 0.5 mg/day in any one week. Do not exceed 10 mg/day or 2.5 mg in a single dose. (2.2)
- Moderate hepatic impairment: Start with 0.5 mg per day. (2.3)

3 DOSAGE FORMS AND STRENGTHS

Capsules: 0.5 mg. (3)

4 CONTRAINDICATIONS

None. (4)

4 CONTRAINDICATIONS

None. (4)

5 WARNINGS AND PRECAUTIONS

- Cardiovascular Toxicity: QT prolongation and ventricular tachycardia have been reported with AGRYLIN. Obtain a pre-treatment cardiovascular examination including an ECG in all patients. Monitor patients for cardiovascular effects. (5.1)
- Pulmonary Hypertension: Assess underlying cardiopulmonary disease prior to initiating therapy. (5.2)
- Bleeding Risk: Monitor patients for bleeding, including those receiving concomitant therapy with other drugs known to cause bleeding. (5.3)

6 ADVERSE REACTIONS

The most common adverse reactions (incidence ≥ 5%) are headache, palpitations, diarrhea, asthenia, edema, nausea, abdominal pain, dizziness, pain, dyspnea, cough, flatulence, vomiting, fever, peripheral edema, rash, chest pain, anorexia, tachycardia, malaise, paresthesia, back pain, pruritus, and dyspepsia. (6.1)
To report SUSPECTED ADVERSE REACTIONS, contact Takeda Pharmaceuticals U.S.A., Inc. at 1-877-TAKEDA-7 (1-877-825-3327)- or FDA at 1-800-FDA-1088 or www.fda.gov/medwatch.

7 DRUG INTERACTIONS

- Other PDE3 inhibitors: Exacerbation of inotropic effects. (7.2)
- Aspirin and Drugs that Increase Bleeding Risk: Increased risk of bleeding with concomitant use. (7.3)

8 USE IN SPECIFIC POPULATIONS

Lactation: Advise not to breastfeed. (8.2)

FULL PRESCRIBING INFORMATION

1 INDICATIONS AND USAGE

AGRYLIN is indicated for the treatment of patients with thrombocythemia, secondary to myeloproliferative neoplasms, to reduce the elevated platelet count and the risk of thrombosis and to ameliorate associated symptoms including thrombo-hemorrhagic events.

2 DOSAGE AND ADMINISTRATION

2.1 Recommended Starting Dosage

Adults: The recommended starting dosage of AGRYLIN is 0.5 mg four times daily or 1 mg twice daily.

Pediatric Patients: The recommended starting dosage of AGRYLIN is 0.5 mg daily.

2.2 Dose Titration Based Upon Platelet Response

Continue the starting dose for at least one week and then titrate to reduce and maintain the platelet count below 600,000/µL, and ideally between 150,000/µL and 400,000/µL. The dose increment should not exceed 0.5 mg/day in any one week. Dosage should not exceed 10 mg/day or 2.5 mg in a single dose. Most patients will experience an adequate response at a dose of 1.5 to 3.0 mg/day. Monitor platelet counts weekly during titration then monthly or as necessary.

2.3 Dose Modifications for Hepatic Impairment

In patients with moderate hepatic impairment (Child Pugh score 7-9) start AGRYLIN therapy at a dose of 0.5 mg/day and monitor frequently for cardiovascular events [see Warnings and Precautions (5.1), Use in Specific Populations (8.6) and Clinical Pharmacology (12.3)]. Patients with moderate hepatic impairment who have tolerated AGRYLIN therapy for one week may have their dose increased. The dose increase increment should not exceed 0.5 mg/day in any one week. Avoid use of AGRYLIN in patients with severe hepatic impairment.

2.4 Clinical Monitoring

AGRYLIN therapy requires clinical monitoring, including complete blood counts, assessment of hepatic and renal function, and electrolytes.

To prevent the occurrence of thrombocytopenia, monitor platelet counts every two days during the first week of treatment and at least weekly thereafter until the maintenance dosage is reached. Typically, platelet counts begin to respond within 7 to 14 days at the proper dosage. In the clinical trials, the time to complete response, defined as platelet count ≤600,000/µL, ranged from 4 to 12 weeks. In the event of dosage interruption or treatment withdrawal, the rebound in platelet count is variable, but platelet counts typically will start to rise within 4 days and return to baseline levels in one to two weeks, possibly rebounding above baseline values. Monitor platelet counts frequently.

3 DOSAGE FORMS AND STRENGTHS

Capsules: White, opaque capsule, imprinted with " 063" in black ink. Each capsule contains 0.5 mg anagrelide equivalent to 0.61 mg anagrelide hydrochloride USP.

4 CONTRAINDICATIONS

None.

4 CONTRAINDICATIONS

None.

5 WARNINGS AND PRECAUTIONS

5.1 Cardiovascular Toxicity

Torsades de pointes and ventricular tachycardia have been reported with AGRYLIN. Obtain a pre-treatment cardiovascular examination including an ECG in all patients. During treatment with AGRYLIN monitor patients for cardiovascular effects and evaluate as necessary.

AGRYLIN increases the QTc interval of the electrocardiogram and increases the heart rate in healthy volunteers [see Clinical Pharmacology (12.2)].

Do not use AGRYLIN in patients with known risk factors for QT interval prolongation, such as congenital long QT syndrome, a known history of acquired QTc prolongation, medicinal products that can prolong QTc interval and hypokalemia [see Drug Interactions (7.1)].

Hepatic impairment increases anagrelide exposure and could increase the risk of QTc prolongation. Monitor patients with hepatic impairment for QTc prolongation and other cardiovascular adverse reactions. The potential risks and benefits of AGRYLIN therapy in a patient with mild and moderate hepatic impairment should be assessed before treatment is commenced. Reduce AGRYLIN dose in patients with moderate hepatic impairment. Avoid use of AGRYLIN in patients with severe hepatic impairment.

In patients with heart failure, bradyarrhythmias, or electrolyte abnormalities, consider periodic monitoring with electrocardiograms [see Clinical Pharmacology (12.2)].

AGRYLIN is a phosphodiesterase 3 (PDE3) inhibitor and may cause vasodilation, tachycardia, palpitations, and congestive heart failure. Other drugs that inhibit PDE3 have caused decreased survival when compared with placebo in patients with Class III-IV congestive heart failure [see Drug Interactions (7.2)].

In patients with cardiac disease, use AGRYLIN only when the benefits outweigh the risks.

5.2 Pulmonary Hypertension

Cases of pulmonary hypertension have been reported in patients treated with AGRYLIN. Evaluate patients for signs and symptoms of underlying cardiopulmonary disease prior to initiating and during AGRYLIN therapy [see Adverse Reactions (6.1)].

5.3 Bleeding Risk

Use of concomitant AGRYLIN and aspirin increased major hemorrhagic events in a postmarketing study. Assess the potential risks and benefits for concomitant use of AGRYLIN with aspirin, since bleeding risks may be increased. Monitor patients for bleeding, including those receiving concomitant therapy with other drugs known to cause bleeding (e.g., anticoagulants, PDE3 inhibitors, NSAIDs, antiplatelet agents, selective serotonin reuptake inhibitors) [see Drug Interactions (7.3), Clinical Pharmacology (12.3)].

5.4 Pulmonary Toxicity

Interstitial lung diseases (including allergic alveolitis, eosinophilic pneumonia and interstitial pneumonitis) have been reported to be associated with the use of AGRYLIN in post-marketing reports. Most cases presented with progressive dyspnea with lung infiltrations. The time of onset ranged from 1 week to several years after initiating AGRYLIN. If suspected, discontinue AGRYLIN and evaluate. Symptoms may improve after discontinuation [see Adverse Reactions (6)].

6 ADVERSE REACTIONS

The following clinically significant adverse reactions are discussed in greater detail in other sections of the labeling:

- Cardiovascular Toxicity [see Warnings and Precautions (5.1)]
- Pulmonary Hypertension [see Warnings and Precautions (5.2)]
- Bleeding Risk [see Warnings and Precautions (5.3)]
- Pulmonary Toxicity [see Warnings and Precautions (5.4)]

6.1 Clinical Trials Experience

Because clinical trials are conducted under widely varying conditions, adverse reaction rates observed in the clinical trials of a drug cannot be directly compared to rates in the clinical trials of another drug and may not reflect the rates observed in practice.

Clinical Studies in Adult Patients

In three single-arm clinical studies, 942 patients [see Clinical Trials (14)] diagnosed with myeloproliferative neoplasms of varying etiology (ET: 551; PV: 117; OMPN: 274) were exposed to AGRYLIN with a mean duration of approximately 65 weeks. Serious adverse reactions reported in these patients included the following: congestive heart failure, myocardial infarction, cardiomyopathy, cardiomegaly, complete heart block, atrial fibrillation, cerebrovascular accident, pericardial effusion [see Warnings and Precautions (5.1)], pleural effusion, pulmonary infiltrates, pulmonary fibrosis, pulmonary hypertension, and pancreatitis. Of the 942 patients treated with AGRYLIN, 161 (17%) were discontinued from the study because of adverse reactions or abnormal laboratory test results. The most common adverse reactions resulting in treatment discontinuation were headache, diarrhea, edema, palpitations, and abdominal pain.

The most frequently reported adverse reactions to AGRYLIN (in 5% or greater of 942 patients with myeloproliferative neoplasms) in clinical trials were listed in Table 1.

Table 1 Adverse Reactions Reported in Clinical Studies of AGRYLIN in at least 5% of Patients
Adverse Reactions | AGRYLIN (N=942) (%)
Cardiac disorders
Palpitations | 26%
Tachycardia | 8%
Chest pain | 8%
General disorders and administration site conditions
Asthenia | 23%
Edema | 21%
Pain | 15%
Fever | 9%
Peripheral edema | 9%
Malaise | 6%
Gastrointestinal disorders
Diarrhea | 26%
Nausea | 17%
Abdominal pain | 16%
Vomiting | 10%
Flatulence | 10%
Anorexia | 8%
Dyspepsia | 5%
Respiratory, thoracic and mediastinal disorders
Dyspnea | 12%
Cough | 6%
Skin and subcutaneous tissue disorders
Rash | 8%
Pruritus | 6%
Musculoskeletal and connective tissue disorders
Back pain | 6%
Nervous system disorders
Headache | 44%
Dizziness | 15%
Paresthesia | 6%

Adverse Reactions (frequency 1% to < 5%) included:

General disorders and administration site conditions: Flu symptoms, chills.

Cardiac disorders: Arrhythmia, angina pectoris, heart failure, syncope.

Vascular disorders: Hemorrhage, hypertension, postural hypotension, vasodilatation.

Gastrointestinal disorders: Constipation, gastrointestinal hemorrhage, gastritis.

Blood and lymphatic system disorders: Anemia, thrombocytopenia, ecchymosis.

Hepatobiliary disorders: Elevated liver enzymes.

Musculoskeletal and connective tissue disorders: Arthralgia, myalgia.

Psychiatric disorders: Depression, confusion, nervousness.

Nervous system disorders: Somnolence, insomnia, amnesia, migraine headache.

Respiratory, thoracic and mediastinal disorders: Epistaxis, pneumonia.

Skin and subcutaneous tissue disorders: Alopecia.

Eye disorders: Abnormal vision, diplopia.

Ear and labyrinth disorders: Tinnitus.

Renal and urinary disorders: Hematuria, renal failure.

Other less frequent adverse reactions (<1%) were:

Cardiac disorders: Ventricular tachycardia, supraventricular tachycardia.

Nervous system disorders: Hypoesthesia.

Clinical Study in Pediatric Patients

The frequency of adverse reactions observed in pediatric patients was similar to adult patients. The most common adverse reactions observed in pediatric patients were fever, epistaxis, headache, and fatigue during the 3-month AGRYLIN treatment in the study. Episodes of increased pulse and decreased systolic or diastolic blood pressure beyond the normal ranges in the absence of clinical symptoms were observed. Other adverse reactions reported in these pediatric patients receiving AGRYLIN treatment were palpitations, headache, nausea, vomiting, abdominal pain, back pain, anorexia, fatigue, and muscle cramps.

6.2 Postmarketing Experience

The following adverse reactions have been identified during post-marketing use of AGRYLIN. Because these reactions are reported voluntarily from a population of uncertain size, it is not always possible to reliably estimate their frequency or establish a causal relationship to drug exposure.

Cardiac disorders: Prinzmetal angina, Torsades de pointes.

Respiratory, thoracic, and mediastinal disorders: Interstitial lung diseases (including allergic alveolitis, eosinophilic pneumonia, and interstitial pneumonitis) [see Warnings and Precautions (5.4)].

Renal and urinary disorders: Tubulointerstitial nephritis.

Hepatobiliary disorders: Clinically significant hepatotoxicity (including symptomatic ALT and AST elevations and elevations greater than three times the ULN).

Nervous system disorders: Cerebral infarction

Other adverse reactions in pediatric patients reported in spontaneous reports and literature reviews include:

Blood and lymphatic system disorders: Anemia.

Skin and subcutaneous tissue disorders: Cutaneous photosensitivity.

Investigations: Elevated leukocyte count.

7 DRUG INTERACTIONS

7.1 Drugs that Prolong QT

Avoid use of AGRYLIN in patients taking medications that may prolong QT interval (including, but not limited to, chloroquine, clarithromycin, haloperidol, methadone, moxifloxacin, amiodarone, disopyramide, procainamide, and pimozide) [see Warnings and Precautions (5.1) and Clinical Pharmacology (12.2)].

7.2 PDE3 Inhibitors

AGRYLIN is a phosphodiesterase 3 (PDE3) inhibitor. Avoid use of drug products with similar properties such as inotropes and other PDE3 inhibitors (e.g., cilostazol, milrinone) [see Warnings and Precautions (5.1) and Clinical Pharmacology (12.2)].

7.3 Aspirin and Drugs that Increase Bleeding Risk

Co-administration of single-dose or repeat-dose AGRYLIN and aspirin showed greater ex vivo anti-platelet aggregation effects than administration of aspirin alone [see Clinical Pharmacology (12.3)]. Results from an observational study in patients with essential thrombocythemia suggest the rate of major hemorrhagic events (MHEs) in patients treated with AGRYLIN is higher than in those subjects treated with another cytoreductive treatment. The majority of the major hemorrhagic events occurred in patients who were also receiving concomitant anti-aggregatory treatment (primarily, aspirin). Therefore, the potential risks of the concomitant use of AGRYLIN with aspirin should be assessed, particularly in patients with a high-risk profile for hemorrhage, before treatment is initiated [see Warnings and Precautions (5.3)].

Monitor patients for bleeding, particularly those receiving concomitant therapy with other drugs known to cause bleeding (e.g., anticoagulants, PDE3 inhibitors, NSAIDs, antiplatelet agents, selective serotonin reuptake inhibitors).

7.4 CYP450 Interactions

CYP1A2 inhibitors: AGRYLIN and its active metabolite are primarily metabolized by CYP1A2. Drugs that inhibit CYP1A2 (e.g., fluvoxamine, ciprofloxacin) could increase the exposure of AGRYLIN. Monitor patients for cardiovascular events and titrate doses accordingly when CYP1A2 inhibitors are co-administered.

CYP1A2 inducers: CYP1A2 inducers could decrease the exposure of AGRYLIN. Patients taking concomitant CYP1A2 inducers (e.g., omeprazole) may need to have their dose titrated to compensate for the decrease in AGRYLIN exposure.

CYP1A2 substrates: AGRYLIN demonstrates limited inhibitory activity towards CYP1A2 in vitro and may alter the exposure of concomitant CYP1A2 substrates (e.g., theophylline, fluvoxamine, ondansetron).

8 USE IN SPECIFIC POPULATIONS

8.1 Pregnancy

Risk Summary

Available data from case reports with AGRYLIN use in pregnant women have not identified a drug-associated risk of major birth defects, miscarriage, or adverse maternal or fetal outcomes. In animal embryo-fetal studies, delayed fetal development (delayed skeletal ossification and reduced body weight) was observed in rats administered anagrelide hydrochloride during organogenesis at doses approximately 97 times the maximum clinical dose (10 mg/day) based on body surface area (see Data). There are adverse effects on maternal and fetal outcomes associated with thrombocythemia in pregnancy (see Clinical Considerations).

The estimated background risk of major birth defects and miscarriage for the indicated population is unknown. All pregnancies have a background risk of birth defect, loss, or other adverse outcomes. In the U.S. general population, the estimated background risk of major birth defect and miscarriage in clinically recognized pregnancies is 2% to 4% and 15% to 20%, respectively.

Clinical Considerations

Disease-associated maternal and/or embryo/fetal risk

Thrombotic events, such as stroke, deep vein thrombosis, or myocardial infarction, can be complications of thrombocythemia. Thrombocythemia in pregnancy is associated with an increased risk for miscarriage, stillbirth, and other maternal outcomes, such as preeclampsia.

Data

Animal Data

Anagrelide hydrochloride was administered orally to pregnant rats and rabbits during the period of organogenesis at doses up to 900 mg/kg/day in rats and up to 20 mg/kg/day in rabbits (875 and 39 times, respectively, the maximum clinical dose of 10 mg/day based on body surface area). In rats, developmental delays were observed including reductions in fetal weight at 300 and 900 mg/kg/day and delays in skeletal ossification at doses of 100 mg/kg/day and higher. The dose of 100 mg/kg/day (600 mg/m^2/day) in rats is approximately 97 times the maximum clinical dose based on body surface area. No adverse embryo-fetal effects were detected in rabbits at the highest dose of 20 mg/kg/day (39 times the maximal clinical dose based on body surface area).

In a pre- and post-natal study conducted in female rats, anagrelide hydrochloride administered at oral doses of 60 mg/kg/day (58 times the maximum clinical dose based on body surface area) or higher during organogenesis through lactation produced delay or blockage of parturition, deaths of non-delivering pregnant dams and their fully developed fetuses, and increased mortality in the pups born.

In a placental transfer study, a single oral dose of [^14C]-anagrelide hydrochloride (3 mg/kg) was administered to pregnant rats on gestation Day 17. Drug-related radioactivity was detected in maternal and fetal tissue.

8.2 Lactation

Risk Summary

There is no information regarding the presence of anagrelide in human milk, the effect on the breastfed child, or the effects on milk production. Anagrelide or its metabolites have been detected in the milk of lactating rats (see Data). Because of the potential for serious adverse reactions, including thrombocytopenia, in a breastfed child, advise patients that breastfeeding is not recommended during treatment with AGRYLIN, and for one week following the last dose.

Data

In a rat milk secretion study, a single oral dose of [^14C]-anagrelide hydrochloride (3 mg/kg) was administered to lactating female rats on postnatal Day 10. Drug-related radioactivity was detected in the maternal milk and blood.

8.3 Females and Males of Reproductive Potential

Infertility

Females

Based on findings from animal studies, AGRYLIN may impair female fertility [see Nonclinical Toxicology (13.1)].

8.4 Pediatric Use

The safety and effectiveness of AGRYLIN have been established in pediatric patients 7 years of age and older. There are no data for pediatric patients less than 7 years of age. Use of AGRYLIN in these pediatric patients is supported by evidence from adequate and well controlled studies of AGRYLIN in adults with additional pharmacokinetic, pharmacodynamic, and safety data in 18 pediatric patients aged 7 through 16 years with thrombocythemia secondary to ET [see Dosage and Administration (2.1), Clinical Pharmacology (12.3), and Clinical Studies (14)].

There were no apparent trends or differences in the types of adverse events observed between the pediatric patients compared with those of the adult patients [see Adverse Reactions (6.1)].

8.5 Geriatric Use

Of the 942 subjects in clinical studies of AGRYLIN, 42.1% were 65 years and over, while 14.9% were 75 years and over. No overall differences in safety or effectiveness were observed between these subjects and younger subjects, and other reported clinical experience has not identified differences in response between the elderly and younger patients, but greater sensitivity of some older individuals cannot be ruled out.

8.6 Hepatic Impairment

Hepatic metabolism is the major route of anagrelide clearance. Exposure to anagrelide is increased 8-fold in patients with moderate hepatic impairment [see Clinical Pharmacology (12.3)] and dose reduction is required [see Dosage and Administration (2.3)]. Use of AGRYLIN in patients with severe hepatic impairment has not been studied. Avoid use of AGRYLIN in patients with severe hepatic impairment. The potential risks and benefits of AGRYLIN therapy in a patient with mild and moderate hepatic impairment should be assessed before treatment is commenced. Assess hepatic function before and during AGRYLIN treatment [see Warnings and Precautions (5.1)].

10 OVERDOSAGE

At higher than recommended doses, AGRYLIN has been shown to cause hypotension. There have been postmarketing case reports of intentional overdose with AGRYLIN. Reported symptoms include sinus tachycardia and vomiting. Symptoms resolved with supportive management. Platelet reduction from AGRYLIN therapy is dose-related; therefore, thrombocytopenia, which can potentially cause bleeding, is expected from overdosage.

In case of overdosage, stop AGRYLIN dosing and monitor platelet counts for thrombocytopenia and observe for possible complications such as bleeding. Consider resumption of AGRYLIN dosing once the platelet count returns to the normal range.

11 DESCRIPTION

AGRYLIN (anagrelide hydrochloride) is a platelet-reducing agent. Its chemical name is 6,7-dichloro-1,5-dihydroimidazo[2,1-b]quinazolin-2(3H)-one monohydrochloride monohydrate. The molecular formula is C10H7Cl2N3O∙HCl∙H2O which corresponds to a molecular weight of 310.55. The structural formula is:

Anagrelide hydrochloride is an off-white powder. It is very slightly soluble in water and sparingly soluble in dimethyl sulfoxide and dimethylformamide.

AGRYLIN is supplied as capsules for oral administration, containing 0.5 mg of anagrelide (equivalent to 0.61 mg of anagrelide hydrochloride USP). The capsules also contain anhydrous lactose NF, crospovidone NF, lactose monohydrate NF, magnesium stearate NF, microcrystalline cellulose NF, and povidone NF as inactive ingredients. The capsule shell contains gelatin, titanium dioxide, and black iron oxide.

12 CLINICAL PHARMACOLOGY

12.1 Mechanism of Action

The precise mechanism by which anagrelide reduces blood platelet count is unknown. In cell culture studies, anagrelide suppressed expression of transcription factors including GATA-1 and FOG-1 required for megakaryocytopoiesis, ultimately leading to reduced platelet production.

12.2 Pharmacodynamics

In blood withdrawn from normal volunteers treated with anagrelide, a disruption was found in the postmitotic phase of megakaryocyte development and a reduction in megakaryocyte size and ploidy. At therapeutic doses, anagrelide does not produce significant changes in white cell counts or coagulation parameters, and may have a small, but clinically insignificant effect on red cell parameters. The active metabolite, 3-hydroxy anagrelide, has similar potency and efficacy to that of anagrelide in the platelet lowering effect; however, exposure (measured by plasma AUC) to 3-hydroxy anagrelide is approximately 2-fold higher compared to anagrelide. Anagrelide and 3-hydroxy anagrelide inhibit cyclic AMP phosphodiesterase 3 (PDE3) and 3-hydroxy anagrelide is approximately forty times more potent than anagrelide (IC50s = 0.9 and 36 nM, respectively). PDE3 inhibition does not alter platelet production. PDE3 inhibitors, as a class can inhibit platelet aggregation. However, significant inhibition of platelet aggregation is observed only at doses of anagrelide higher than those typically required to reduce platelet count. PDE3 inhibitors have cardiovascular (CV) effects including vasodilation, positive inotropy and chronotropy.

Cardiac Electrophysiology

The effect of anagrelide dose (0.5 mg and 2.5 mg single doses) on the heart rate and QTc interval prolongation potential was evaluated in a double-blind, randomized, placebo- and active-controlled, cross-over study in 60 healthy adult men and women.

A dose-related increase in heart rate was observed, with the maximum increase occurring around the time of maximal drug concentration (0.5 – 4 hours). The maximum change in mean heart rate occurred at 2 hours after administration and was +7.8 beats per minute (bpm) for 0.5 mg and +29.1 bpm for 2.5 mg.

Dose-related increase in mean QTc was observed. The maximum mean (95% upper confidence bound) change in QTcI (individual subject correction) from placebo after baseline-correction was 7.0 (9.8) ms and 13.0 (15.7) ms following anagrelide doses of 0.5 mg and 2.5 mg, respectively.

12.3 Pharmacokinetics

Dose proportionality has been found in the dose range 0.5 mg to 2.5 mg.

Absorption

Following oral administration of AGRYLIN, at least 70% is absorbed from the gastrointestinal tract. In fasted subjects, anagrelide peak plasma concentrations occur within about 1 hour after administration.

Pharmacokinetic data obtained from healthy volunteers comparing the pharmacokinetics of anagrelide in the fed and fasted states showed that administration of a 1 mg dose of anagrelide with food decreased the Cmax by 14%, but increased the AUC by 20%. Food decreased the Cmax of the active metabolite 3-hydroxy anagrelide by 29%, although it had no effect on the AUC.

Elimination

Anagrelide and 3-hydroxy anagrelide are eliminated with plasma half-lives of approximately 1.5 and 2.5 hours, respectively. Anagrelide and 3-hydroxy anagrelide do not accumulate in plasma when the clinical dose regimens are administered.

Metabolism: Anagrelide is primarily metabolized by CYP1A2 to the active metabolite, 3-hydroxy anagrelide, which is subsequently metabolized by CYP1A2 to the inactive metabolite, RL603. Less than 1% of the administered dose is recovered in the urine as anagrelide, and approximately 3% and 16-20% of the administered dose is recovered as 3-hydroxy anagrelide and RL603, respectively.

Drug Interactions

Aspirin: In two pharmacodynamic interaction studies in healthy subjects, co-administration of single-dose anagrelide 1 mg and aspirin 900 mg or repeat-dose anagrelide 1 mg once daily and aspirin 75 mg once daily showed greater ex vivo anti-platelet aggregation effects than administration of aspirin alone. Co-administered anagrelide 1 mg and aspirin 900 mg single-doses had no effect on bleeding time, prothrombin time (PT) or activated partial thromboplastin time (aPTT).

Digoxin or warfarin: In vivo interaction studies in humans have demonstrated that anagrelide does not affect the pharmacokinetic properties of digoxin or warfarin, nor does digoxin or warfarin affect the pharmacokinetic properties of anagrelide.

Specific Populations

Pediatric: Dose-normalized Cmax and AUC of anagrelide were higher in children and adolescents (age range 7 through 16 years) with essential thrombocythemia, by 17% and 56%, respectively, than in adult patients (19 through 57 years).

Geriatric: Cmax and AUC of anagrelide were 36% and 61% higher, respectively, in elderly patients (age range 65 through 75 years), than in younger adults (age range 22 through 50 years), but Cmax and AUC of the active metabolite, 3-hydroxy anagrelide, were 42% and 37% lower, respectively, in the elderly patients.

Renal Impairment: Pharmacokinetic study at a single dose of 1 mg anagrelide in subjects with severe renal impairment (creatinine clearance <30 mL/min) showed no significant effects on the pharmacokinetics of anagrelide.

Hepatic Impairment: A pharmacokinetic study at a single dose of 1 mg anagrelide in subjects with moderate hepatic impairment (Child Pugh score 7-9) showed a 2-fold increase in mean anagrelide Cmax and an 8-fold increase in total exposure (AUC) to anagrelide compared with healthy subjects. Additionally, subjects with moderate hepatic impairment showed 24% lower mean 3-hydroxy anagrelide Cmax and 77% higher mean 3-hydroxy anagrelide AUC compared to healthy subjects.

13 NONCLINICAL TOXICOLOGY

13.1 Carcinogenesis, Mutagenesis, Impairment of Fertility

In a two-year rat carcinogenicity study a higher incidence of uterine adenocarcinoma, relative to controls, was observed in females receiving 30 mg/kg/day (at least 174 times human AUC exposure after a 1 mg twice daily dose). Adrenal pheochromocytomas were increased relative to controls in males receiving 3 mg/kg/day and above, and in females receiving 10 mg/kg/day and above (at least 10 and 18 times respectively human AUC exposure after a 1 mg twice daily dose).

Anagrelide hydrochloride was not mutagenic in the bacterial mutagenesis (Ames) assay or the mouse lymphoma cell (L5178Y, TK+/-) forward mutation assay, and was not clastogenic in the in vitro chromosome aberration assay using human lymphocytes or the in vivo mouse micronucleus test.

Anagrelide hydrochloride at oral doses up to 240 mg/kg/day (233 times the recommended human dose of 10 mg/day based on body surface area) had no effect on fertility and reproductive function of male rats. However, in fertility studies in female rats, oral doses of 30 mg/kg/day (29 times the recommended maximum human dose based on body surface area) or higher resulted in increased pre- and post-implantation loss and a decrease in the number of live embryos.

13.2 Animal Toxicology and/or Pharmacology

In the 2-year rat study, a significant increase in non-neoplastic lesions was observed in anagrelide treated males and females in the adrenal (medullary hyperplasia), heart (myocardial hypertrophy and chamber distension), kidney (hydronephrosis, tubular dilation and urothelial hyperplasia), and bone (femur enostosis). Vascular effects were observed in tissues of the pancreas (arteritis/periarteritis, intimal proliferation, and medial hypertrophy), kidney (arteritis/periarteritis, intimal proliferation, and medial hypertrophy), sciatic nerve (vascular mineralization), and testes (tubular atrophy and vascular infarct) in anagrelide-treated males.

14 CLINICAL STUDIES

Clinical Studies in Adult Patients:

A total of 942 patients with myeloproliferative neoplasms including 551 patients with Essential Thrombocythemia (ET), 117 patients with Polycythemia Vera (PV), 178 patients with Chronic Myelogenous Leukemia (CML), and 96 patients with other myeloproliferative neoplasms (OMPN), were treated with AGRYLIN in three clinical trials. Patients with OMPN included 87 patients who had Myeloid Metaplasia with Myelofibrosis (MMM), and 9 patients who had unclassified myeloproliferative neoplasms.

Patients were enrolled in clinical trials if their platelet count was ≥900,000/µL on two occasions or ≥650,000/µL on two occasions with documentation of symptoms associated with thrombocythemia. The mean duration of AGRYLIN therapy for ET, PV, CML, and OMPN patients was 65, 67, 40, and 44 weeks, respectively; 23% of patients received treatment for 2 years. Patients were treated with AGRYLIN starting at doses of 0.5-2.0 mg every 6 hours. The dose was increased if the platelet count was still high, but to no more than 12 mg each day. Efficacy was defined as reduction of platelet count to or near physiologic levels (150,000-400,000/µL). The criteria for defining subjects as "responders" were reduction in platelets for at least 4 weeks to ≤600,000/µL, or by at least 50% from baseline value. Subjects treated for less than 4 weeks were not considered evaluable. The results are depicted graphically below:

 |  | Time on Treatment
 |  |  | Weeks |  |  |  | Years
 | Baseline | 4 | 12 | 24 | 48 |  | 2 | 3 | 4
Mean [x 10^3/µL] | 1131 | 683 | 575 | 526 | 484 |  | 460 | 437 | 457
N | 923 [Nine hundred and forty-two subjects with myeloproliferative neoplasms were enrolled in three research studies. Of these, 923 had platelet counts measured over the duration of the studies.] | 868 | 814 | 662 | 530 |  | 407 | 207 | 55

AGRYLIN was effective in phlebotomized patients as well as in patients treated with other concomitant therapies including hydroxyurea, aspirin, interferon, radioactive phosphorus, and alkylating agents.

Clinical Study in Pediatric Patients:

An open-label safety and PK/PD study was conducted in 18 pediatric patients 7 through 16 years of age (8 children 7 through 11 years of age and 10 adolescents 12 through 16 years of age, mean age of 12 years; 8 males and 10 females) with thrombocythemia secondary to ET as compared to 17 adult patients (mean age of 66 years, 9 males and 8 females). Prior to entry on to the study, 17 of 18 pediatric patients and 12 of 17 adult patients had received AGRYLIN treatment for an average of 2 years. The median starting total daily dose, determined by retrospective chart review, for pediatric and adult patients with ET who had received AGRYLIN prior to study entry was 1 mg for each of the three age groups (7 through 11 and 12 through 16 years of age and adults). The starting dose for 6 AGRYLIN-naive patients at study entry was 0.5 mg once daily. At study completion, the median total daily maintenance doses were similar across age groups, median of 1.75 mg for children of 7 through 11 years of age, 2.25 mg in adolescents 12 through 16 years of age, and 1.5 mg for adults.

16 HOW SUPPLIED/STORAGE AND HANDLING

AGRYLIN is available as:

0.5 mg, opaque, white capsules imprinted " 063" in black ink: NDC 54092-063-01 = bottle of 100

STORAGE AND HANDLING

Store at 25°C (77°F) excursions permitted to 15°C to 30°C (59°F to 86°F), [See USP Controlled Room Temperature]. Store in a light resistant container.

17 PATIENT COUNSELING INFORMATION

- Dose: Tell the patient that their dose will be adjusted on a weekly basis until they are on a dose that lowers their platelets to an appropriate level. This will also help the patient to adjust to common side effects. Tell the patient to contact their doctor if they experience tolerability issues, so the dose or dosing frequency can be adjusted [see Dosage and Administration (2)].
- Cardiovascular effects: Tell the patient to contact a doctor immediately if they experience chest pain, palpitations, or feel their heartbeat is irregular [see Warnings and Precautions (5.1)].
- Risk of Pulmonary Hypertension: Tell the patient to contact a doctor immediately if they experience shortness of breath, swelling in legs or ankles, or lips and skin turn a bluish color [see Warnings and Precautions (5.2)].
- Risk of bleeding: Warn the patient that concomitant aspirin (or other medicines that affect blood clotting) may increase the risk of bleeding. Tell the patient to contact a doctor immediately if they experience signs or symptoms of bleeding (e.g., vomit blood, pass bloody or black stools) or experience unexplained bruising/bruise more easily than usual [see Warnings and Precautions (5.3), Drug Interactions (7.1)].
- Lactation: Advise patients not to breastfeed during treatment with AGRYLIN, and for one week following the last dose [see Use in Specific Populations (8.2)].
- Infertility: Advise females of reproductive potential treatment with AGRYLIN may impair fertility [see Use in Specific Populations (8.3), Nonclinical Toxicology (13.1)].

Distributed by:
Takeda Pharmaceuticals America, Inc.
Cambridge, MA 02142

AGRYLIN is a registered trademark of Takeda Pharmaceuticals U.S.A., Inc.

© 2024 Takeda Pharmaceuticals U.S.A., Inc. All rights reserved.

PRINCIPAL DISPLAY PANEL - 0.5 mg Capsule Bottle Label

063-01
NDC 54092-063-01

Agrylin
(anagrelide) Capsules
Platelet-reducing Agent

100 CAPSULES

Rx only

0.5 mg

Takeda